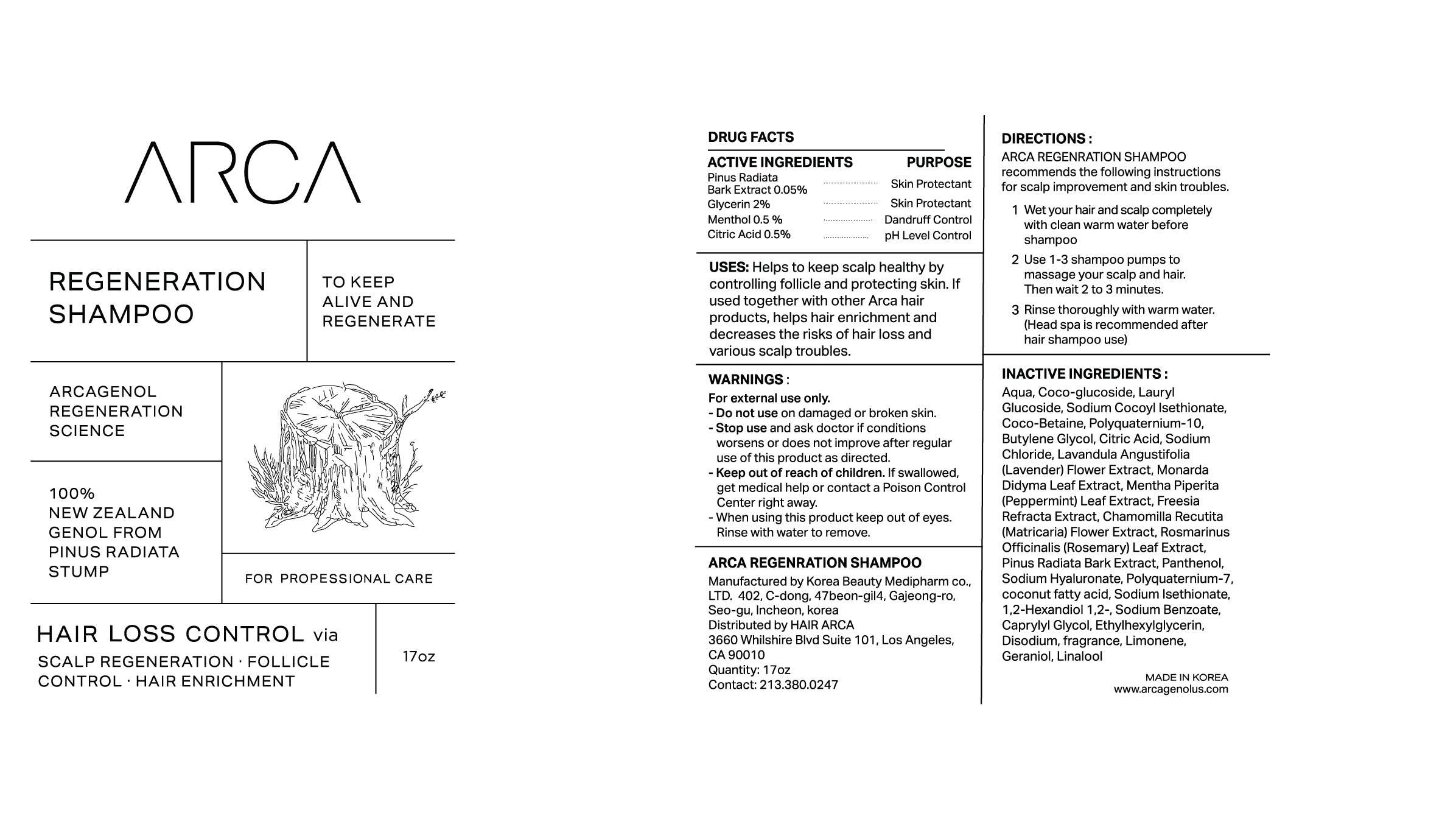 DRUG LABEL: ARCA RegnerationShampoo
NDC: 83104-401 | Form: SHAMPOO
Manufacturer: Hair Arca, Inc
Category: otc | Type: HUMAN OTC DRUG LABEL
Date: 20221004

ACTIVE INGREDIENTS: GLYCERIN 2 g/100 mL; MENTHOL 0.5 g/100 mL; PINUS RADIATA BARK 0.05 g/100 mL; CITRIC ACID MONOHYDRATE 0.5 g/100 mL
INACTIVE INGREDIENTS: POLYQUATERNIUM-7 (70/30 ACRYLAMIDE/DADMAC; 1600 KD); FRAGRANCE LEMON ORC2001060; FREESIA ALBA FLOWER; MONARDA DIDYMA LEAF; SODIUM CHLORIDE; CHAMOMILE; SODIUM COCOYL ISETHIONATE; POLYQUATERNIUM-10 (400 CPS AT 2%); HYALURONATE SODIUM; LAURYL GLUCOSIDE; COCO GLUCOSIDE; COCO-BETAINE; LAVANDULA ANGUSTIFOLIA FLOWER; SODIUM ISETHIONATE; 1,2-HEXANEDIOL; EDETATE DISODIUM; CAPRYLYL GLYCOL; COCONUT ACID; ETHYLHEXYLGLYCERIN; LIMONENE, (+)-; GERANIOL; LINALOOL, (+/-)-; PANTHENOL; WATER; BUTYLENE GLYCOL; ROSEMARY; MENTHA PIPERITA LEAF; SODIUM BENZOATE

83104-401 ARCA Regeneration Shampoo

Active ingredients

Pinus Radiata Bark Extract 0.05%
Glycerin 2%
Menthol 0.5 %
Citric Acid 0.5%

Purpose

Pinus Radiata Bark Extract 0.05% - Skin Protectant
Glycerin 2% - Skin Protectant
Menthol 0.5 % - Dandruff Control
Citric Acid 0.5% - pH Level Control

Uses

Helps to keep scalp healthy by controlling follicle and protecting skin.

If used together with other Arca hair products, helps hair enrichment and decreases the risks of hair loss and various scalp troubles.

Warnings

For external use only.

Warnings

When using this product keep out of eyes.
Rinse with water to remove.

Warnings

Stop use and ask doctor if conditions worsens or does not improve after regular use of this product as directed.

Warnings

Keep out of reach of children.

If swallowed, get medical help or contact a Poison Control Center right away.

Warnings

Do not use on damaged or broken skin.

Directions

ARCA REGENRATION SHAMPOO recommends the following instructions for scalp improvement and skin troubles.

1 Wet your hair and scalp completely with clean warm water before shampoo
2 Use 1-3 shampoo pumps to massage your scalp and hair.
Then wait 2 to 3 minutes.
3 Rinse thoroughly with warm water.
(Head spa is recommended after hair shampoo use)

Inactive ingredients

Aqua, Coco-glucoside, Lauryl Glucoside, Sodium Cocoyl Isethionate, Coco-Betaine, Polyquaternium-10, Butylene Glycol, Citric Acid, Sodium Chloride, Lavandula Angustifolia (Lavender) Flower Extract, Monarda Didyma Leaf Extract, Mentha Piperita (Peppermint) Leaf Extract, Freesia Refracta Extract, Chamomilla Recutita (Matricaria) Flower Extract, Rosmarinus Officinalis (Rosemary) Leaf Extract, Pinus Radiata Bark Extract, Panthenol, Sodium Hyaluronate, Polyquaternium-7, coconut fatty acid, Sodium Isethionate, 1,2-Hexandiol 1,2-, Sodium Benzoate, Caprylyl Glycol, Ethylhexylglycerin, Disodium, fragrance, Limonene, Geraniol, Linalool

Display Panel

83104-401